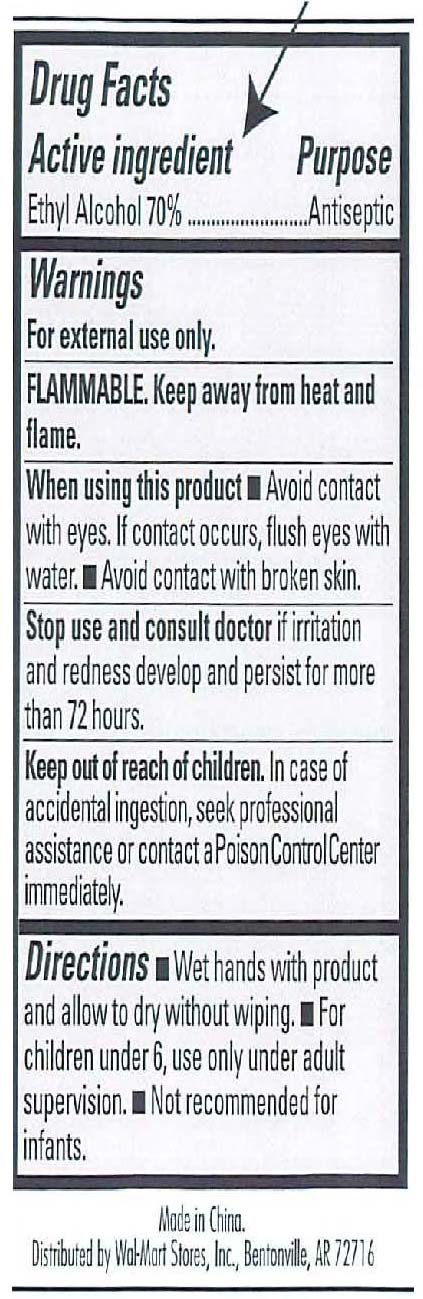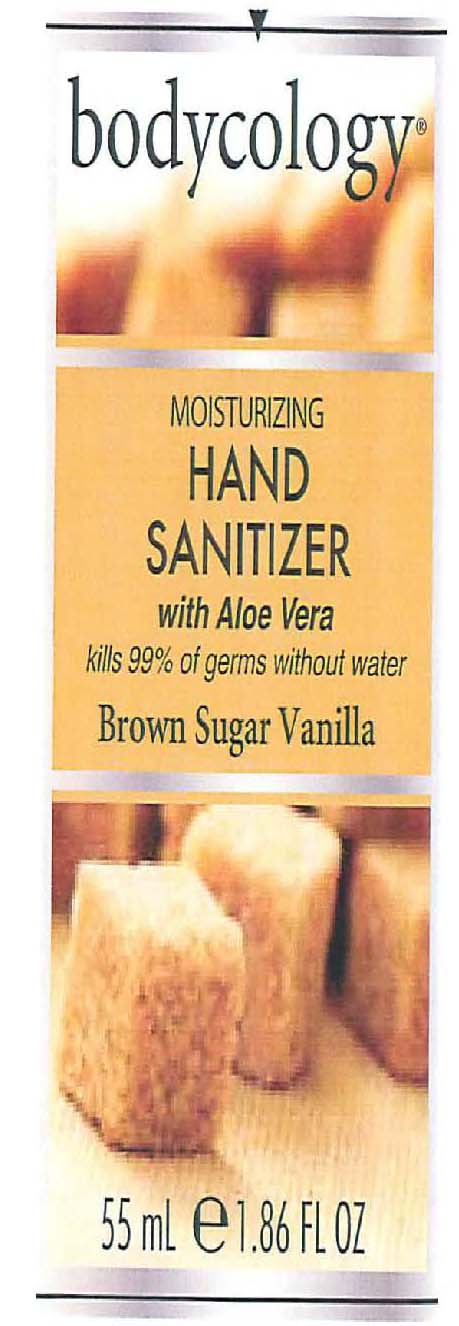 DRUG LABEL: Bodycology
NDC: 51706-301 | Form: CREAM
Manufacturer: Landy International
Category: otc | Type: HUMAN OTC DRUG LABEL
Date: 20100701

ACTIVE INGREDIENTS: ALCOHOL 70 mL/100 mL

Moisturizing Hand Sanitizer Brown Sugar Vanilla

Active Ingredients Purpose

Alcohol 70% Antiseptic

Warnings

-For external use only.

-Flammable. Keep away from heat and flame

-When using this product avoid contact with eyes. If contact occurs, flush eyes with water. Avoid contact with broken skin

-Stop use and consult doctor if irritation and redness develops and persists for more than 72 hours

-Keep out of reach of children. In case of accidental ingestion, seek professional assistance or contact a Poison Control Center immediately.

Directions:

-Wet hands with product and allow to dry without whiping.

-For children under 6, use only under adult supervision

-Not recommended for infants.

PACKAGE LABEL

Bodycology

Moisturizing Hand Sanitizer

Brown Sugar Vanilla

55 mL/ 1.86 fl. oz.